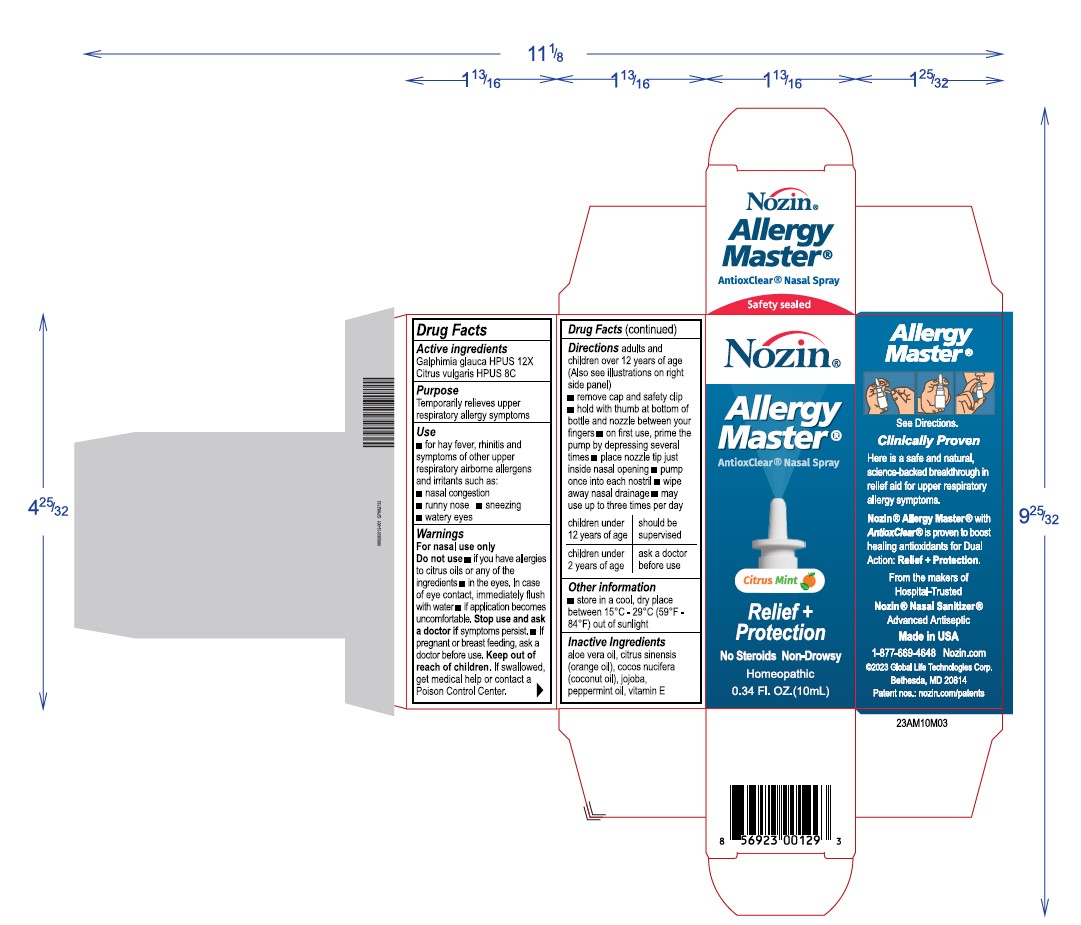 DRUG LABEL: Nozin Allergy Master
NDC: 72363-028 | Form: SPRAY
Manufacturer: AG Essence
Category: homeopathic | Type: HUMAN OTC DRUG LABEL
Date: 20240304

ACTIVE INGREDIENTS: GALPHIMIA GLAUCA WHOLE 0.001 g/10 g; CITRUS AURANTIUM FRUIT OIL 0.001 g/10 g
INACTIVE INGREDIENTS: ALOE VERA WHOLE 0.49 g/10 g; PEPPERMINT OIL 0.075 g/10 g; VITAMIN E POLYETHYLENE GLYCOL SUCCINATE 0.025 g/10 g; ORANGE OIL 0.49 g/10 g; JOJOBA OIL 6.92 g/10 g; COCONUT OIL 2 g/10 g

Directions

Adults and childrenover 12 years of age (Also see illustrations on right side)

- remove cap and safety clip
- hold with thumb at bottomof bottles and nozzle between your fingers
- on first use, prime the pump by depressing several times
- place nozzle tip to just inside nasal opening
- pimp once into each nostril
- wipe away nasal drainage
- may use up to 3 times per day

children under 12 years of age shgould be supervised

children under 2 years of age ask a doctor before use

Other Information

- store in a cool, dry place between 15 and 29 degrees celsius (59 and 84 degrees fahrenheit) out of sunliight

Active Ingredients

Galphimia glauca HPUS 12X

Ctrus Vulgaris HPUS 8C

Inactive Ingredients

aloe vera oil, citrus sinesis (orange oil), cocos nucifera (coconut oil), jojoba, peppermint oil, vitamin E

Purpose

Temporarily relieves upper respiratory allergy symptoms

Warnings

For nasal use only

Do not use

if you have allergies to citrus oild or any of the other ingredients
in the eyes, in case of eye contact, immediately flus with water
if application becomes uncomfortable Stop use and ask a doctor if symptoms persist
if pregnant or breast feeding, ask a doctor before use.

Keep out of reach of children

If swallowed get medical help or contact a Poison Control Center

Use

- for hay fever, rhinitis and symptoms of other upper respiratory airborne allergens and irritants such as
- nasal congestion
- sneezing
- watery eyes